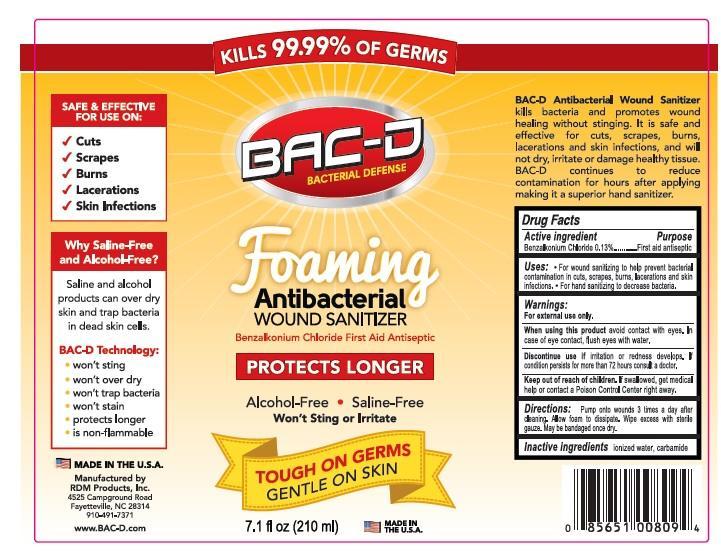 DRUG LABEL: BAC-D Foaming Antibacterial Wound sanitizer
NDC: 69082-700 | Form: LIQUID
Manufacturer: RDM Products, Inc
Category: otc | Type: HUMAN OTC DRUG LABEL
Date: 20151110

ACTIVE INGREDIENTS: BENZALKONIUM CHLORIDE 0.13 g/100 mL
INACTIVE INGREDIENTS: WATER; UREA

BAC-D Foaming Antibacterial Wound sanitizer

Active ingredient

Benzalkonium chloride 0.13 %

Purpose

First aid antiseptic

Keep out of reach of children.

If swallowed, get medical help or contact a Poison Control Center right away.

Uses

First aid to help prevent the risk of bacterial contamination in cuts, scrapes, burns, lacerations and skin infections

Warnings

For external use only.

When using this product avoid contact with eyes. In case of eye contact flush eyes with water .

Stop use and ask a doctor if irritation or redness develops, or if condition persists for more than 72 hours

Directions

- For ages two years and older. Pump a small amount on the area up to 3 times a day. Wipe off excess with sterile Gauze. Once dry, may be covered with a bandage

Inactive ingredients

Ionized water, Carbamide

Made in the U.S.A

Manufactured for

RDM Products Inc.

PO Box 35003

Fayetteville, NC 28303

910-491-7371

www.BAC-D.com